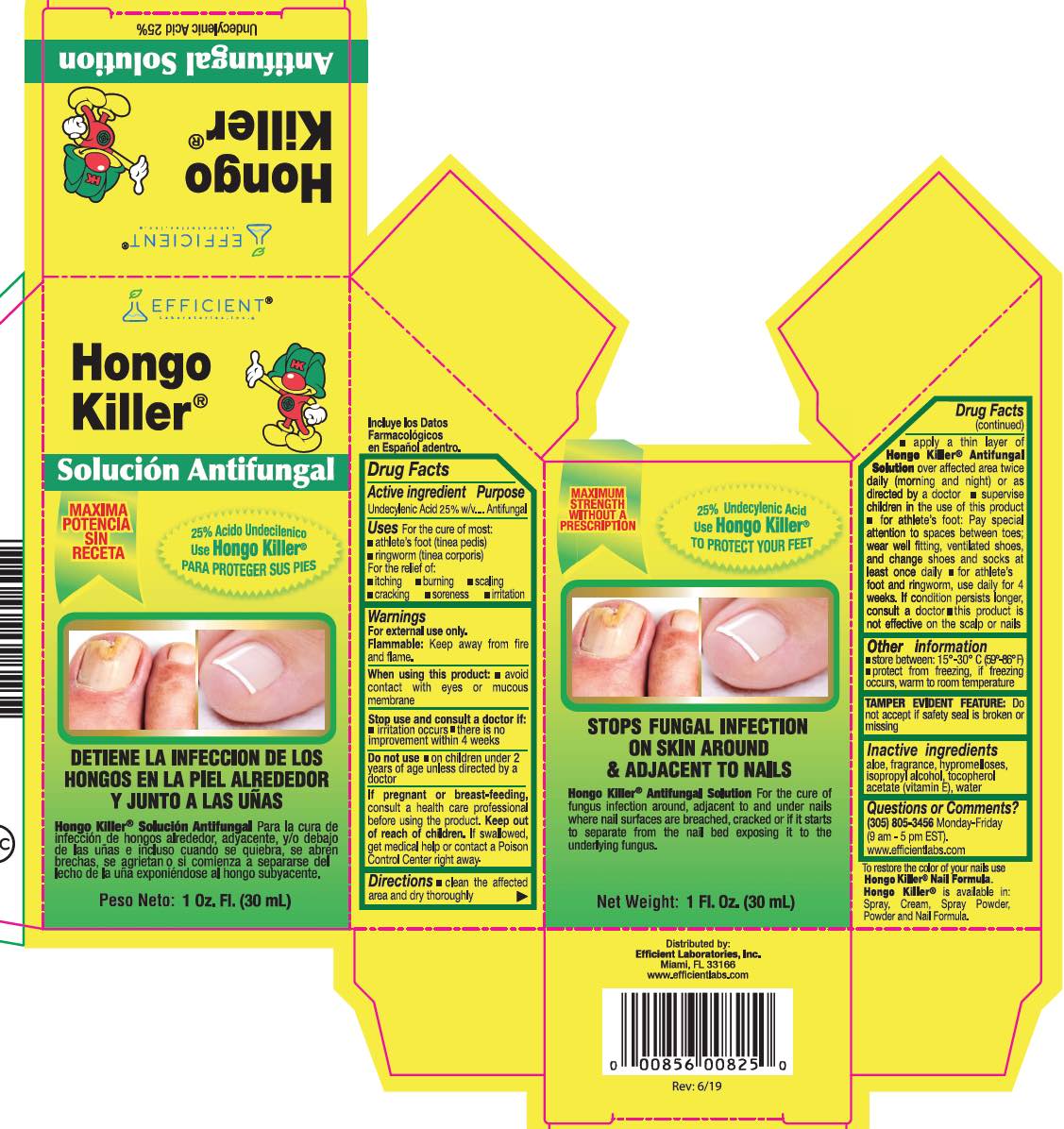 DRUG LABEL: Hongo Killer
NDC: 58593-826 | Form: LIQUID
Manufacturer: Efficient Laboratories Inc
Category: otc | Type: HUMAN OTC DRUG LABEL
Date: 20241014

ACTIVE INGREDIENTS: UNDECYLENIC ACID 25 mg/100 mL
INACTIVE INGREDIENTS: ALOE VERA LEAF; HYPROMELLOSE 2208 (100 MPA.S); ISOPROPYL ALCOHOL; WATER; .ALPHA.-TOCOPHEROL

Drug Facts

Active Ingredient Purpose

Undecylenic Acid 25% w/v ............................. Antifungal

Purpose

Antifungal

Warnings

For external use only

Flammable: Keep away from fire or flame.

When using this product:avoid with eyes or mucous membrane.

Stop use and ask a doctor if:

- irritation occurs
- there is no improvement within 4 weeks

Do not use on children under 2 years of age unless directed by a doctor.

Keep out of reach of children. If swallowed, get medical help or contact a Poison Control Center right away.

PREGNANCY OR BREAST FEEDING

If pregnant or breast-feeding,consult a health care professional before using this product.

Directions
Clean the affected area and dry thoroughly.

- Apply a thin layer of Hongo Killer Antifungal Solution over affected area twice daily (morning and night) or as directed by a doctor.
- Supervise children in the use of this product.
- For athlete’s foot: Pay special attention to spaces between toes; wear well fitting,ventilated shoes, and change shoes and socks at least once daily.
- For athlete’s foot and ringworm, use daily for 4 weeks. If condition persists longer, consult a doctor. This product is not effective on the scalp or nails.

Uses
For the cure of most:

- athlete's foot (tinea pedis)
- ringworm (tinea corporis)

For the relief of:

- itching
- burning
- scaling
- cracking
- soreness
- irritation

Questions or comments?
305-805-3456 (M-F 9:00 am-5:00 pm EST) www.efficientlabs.com

Inactive ingredients
aloe, fragrance, hypromelloses, isopropyl alcohol, tocopherol acetate (Vitamin E), water